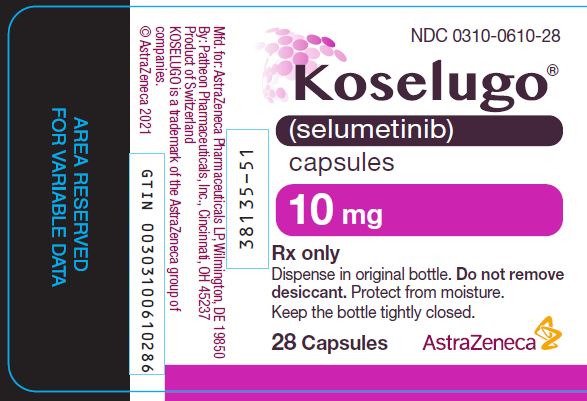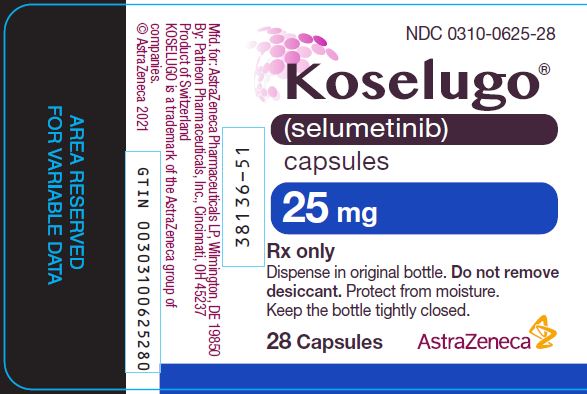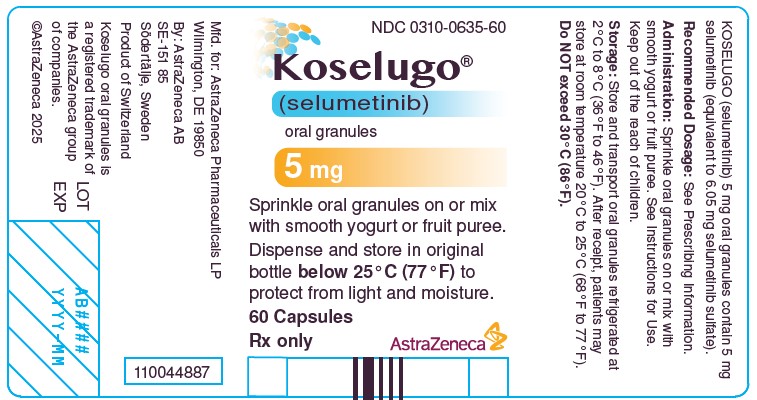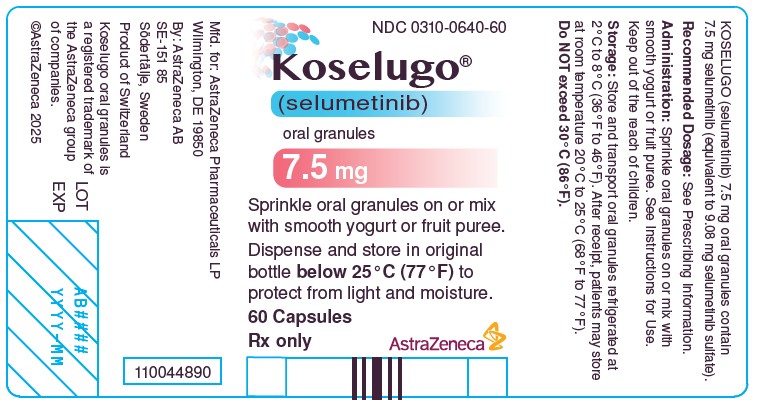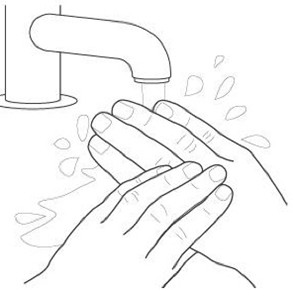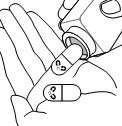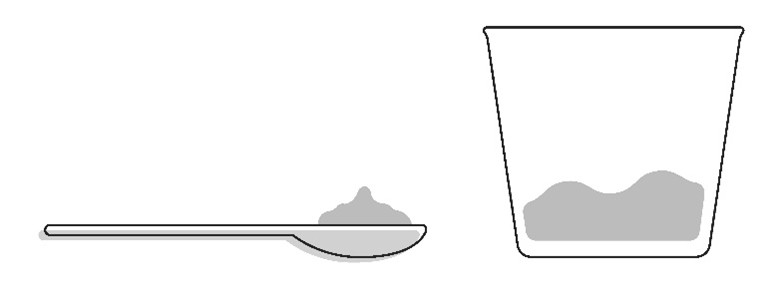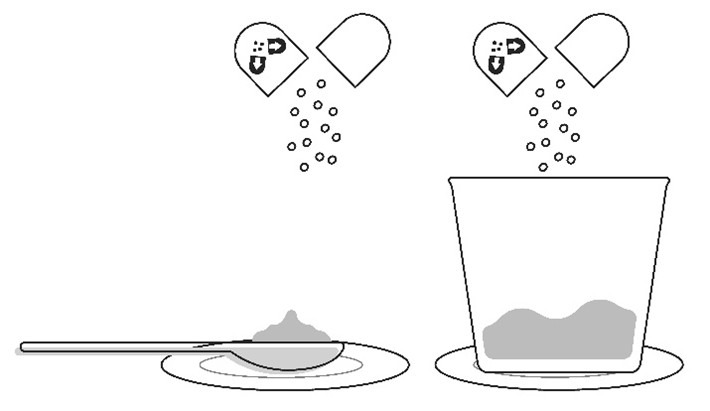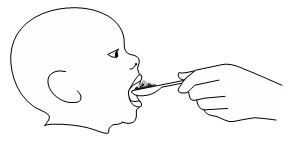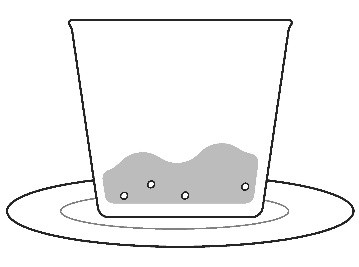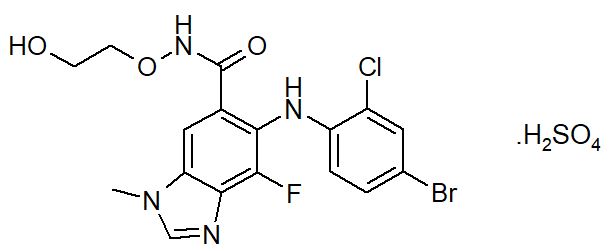 DRUG LABEL: KOSELUGO
NDC: 0310-0610 | Form: CAPSULE
Manufacturer: AstraZeneca Pharmaceuticals LP
Category: prescription | Type: HUMAN PRESCRIPTION DRUG LABEL
Date: 20251119

ACTIVE INGREDIENTS: SELUMETINIB 10 mg/1 1
INACTIVE INGREDIENTS: VITAMIN E POLYETHYLENE GLYCOL SUCCINATE; HYPROMELLOSE, UNSPECIFIED; CARRAGEENAN; POTASSIUM CHLORIDE; TITANIUM DIOXIDE; SHELLAC; ISOPROPYL ALCOHOL; FERROSOFERRIC OXIDE; BUTYL ALCOHOL; PROPYLENE GLYCOL; AMMONIA; WATER

HIGHLIGHTS OF PRESCRIBING INFORMATION

These highlights do not include all the information needed to use KOSELUGO safely and effectively. See full prescribing information for KOSELUGO.
KOSELUGO® (selumetinib) capsules, for oral use
KOSELUGO® (selumetinib) oral granules
Initial U.S. Approval: 2020

RECENT MAJOR CHANGES

Indications and Usage (1) 11/2025

Dosage and Administration (2.1) 11/2025

Warnings and Precautions (5.1, 5.2, 5.3, 5.4, 5.5, 5.7) 11/2025

1 INDICATIONS AND USAGE

KOSELUGO is a kinase inhibitor indicated for the treatment of adult and pediatric patients 1 year of age and older with neurofibromatosis type 1 (NF1) who have symptomatic, inoperable plexiform neurofibromas (PN). (1)

2 DOSAGE AND ADMINISTRATION

- KOSELUGO capsules: The recommended dosage is 25 mg/m^2, swallowed whole, taken orally twice daily with or without food (see Table 1). (2.1, 2.2)
- KOSELUGO oral granules: The recommended dosage is equivalent to 25 mg/m^2, sprinkled onto or mixed with soft food and taken orally twice daily (see Table 2). (2.1, 2.2)
- Moderate hepatic impairment (Child-Pugh B): The recommended dosage is 20 mg/m^2 orally twice daily (see Tables 6 and 7). (2.2, 2.4)
- Severe hepatic impairment (Child-Pugh C): The recommended dosage has not been established. (2.4, 8.6)
- Strong or Moderate CYP3A4 Inhibitors or Fluconazole: If coadministration with strong or moderate CYP3A4 inhibitors or fluconazole cannot be avoided, reduce the dose of KOSELUGO (see Tables 8 and 9). (2.5)

3 DOSAGE FORMS AND STRENGTHS

Capsules: 10 mg and 25 mg of selumetinib. (3)

Oral Granules: 5 mg and 7.5 mg of selumetinib. (3)

4 CONTRAINDICATIONS

None. (4)

5 WARNINGS AND PRECAUTIONS

- Left Ventricular Dysfunction: Assess ejection fraction prior to initiating treatment, every 3 months during the first year, then every 6 months thereafter and as clinically indicated. Withhold, reduce the dose, or permanently discontinue KOSELUGO based on severity of adverse reaction. (2.3, 5.1)
- Ocular Toxicity: Conduct ophthalmic assessments prior to initiating KOSELUGO, at regular intervals during treatment and for new or worsening visual changes. Permanently discontinue KOSELUGO for retinal vein occlusion (RVO). Withhold KOSELUGO for retinal pigment epithelial detachment (RPED), monitor with optical coherence tomography assessments until resolution, and resume at reduced dose. (2.3, 5.2)
- Gastrointestinal Toxicity: Advise patients to start an anti-diarrheal agent immediately after the first episode of loose stool and to increase fluid intake. Withhold, reduce the dose, or permanently discontinue KOSELUGO based on severity of adverse reaction. (2.3, 5.3)
- Skin Toxicity: Monitor for severe skin rashes. Withhold, reduce the dose, or permanently discontinue KOSELUGO based on severity of adverse reaction. (2.3, 5.4)
- Increased Creatine Phosphokinase (CPK): Increased CPK and rhabdomyolysis can occur. Obtain serum CPK prior to initiating KOSELUGO, periodically during treatment, and as clinically indicated. If increased CPK occurs, evaluate for rhabdomyolysis or other causes. Withhold, reduce the dose, or permanently discontinue KOSELUGO based on severity of adverse reaction. (2.3, 5.5)
- Increased Vitamin E Levels and Increased Risk of Bleeding (KOSELUGO Capsules): KOSELUGO capsules contain vitamin E and daily intake of vitamin E that exceeds the recommended or safe limits may increase the risk of bleeding. An increased risk of bleeding may occur in patients co-administered vitamin-K antagonists or anti-platelet agents. KOSELUGO oral granules do not contain vitamin E. (5.6)
- Embryo-Fetal Toxicity: Can cause fetal harm. Advise patients of reproductive potential of the potential risk to a fetus and to use effective contraception (5.7, 8.1, 8.3).

6 ADVERSE REACTIONS

Most common adverse reactions in pediatric patients (≥ 40%) are: vomiting, diarrhea, increased creatine phosphokinase, dry skin, paronychia, nausea, dermatitis acneiform, and pyrexia. (6.1)

Most common adverse reactions in adult patients (≥ 40%) are rash (all), dermatitis acneiform, and diarrhea. (6.1)

To report SUSPECTED ADVERSE REACTIONS, contact AstraZeneca 1-800-236-9933 or FDA at 1-800-FDA-1088 or www.fda.gov/medwatch.

7 DRUG INTERACTIONS

- Strong or Moderate CYP3A4 Inhibitors or Fluconazole: Avoid coadministration of strong or moderate CYP3A4 inhibitors or fluconazole with KOSELUGO. If coadministration cannot be avoided, reduce the dose of KOSELUGO. (2.5, 7.1)
- Strong or Moderate CYP3A4 Inducers: Avoid concomitant use of strong and moderate CYP3A4 inducers. (7.1)

8 USE IN SPECIFIC POPULATIONS

- Lactation: Advise not to breastfeed. (8.2)

FULL PRESCRIBING INFORMATION

1 INDICATIONS AND USAGE

KOSELUGO is indicated for the treatment of adult and pediatric patients 1 year of age and older with neurofibromatosis type 1 (NF1) who have symptomatic, inoperable plexiform neurofibromas (PN) [see Dosage and Administration (2)].

2 DOSAGE AND ADMINISTRATION

2.1 Recommended Dosage

The recommended dosage of KOSELUGO capsules (see Table 1) and KOSELUGO oral granules (see Table 2) for adult and pediatric patients 1 year of age and older, based on body surface area, is 25 mg/m^2 orally twice daily, until disease progression or unacceptable toxicity [see Dosage and Administration (2.2)].

Table 1 Recommended Dosage: KOSELUGO Capsules
Body Surface Area [The recommended dosage of KOSELUGO capsules for patients with a BSA less than 0.55 m^2 has not been established.] | KOSELUGO Capsules
0.55 – 0.69 m^2 | 20 mg in the morning and 10 mg in the evening
0.70 – 0.89 m^2 | 20 mg twice daily
0.90 – 1.09 m^2 | 25 mg twice daily
1.10 – 1.29 m^2 | 30 mg twice daily
1.30 – 1.49 m^2 | 35 mg twice daily
1.50 – 1.69 m^2 | 40 mg twice daily
1.70 – 1.89 m^2 | 45 mg twice daily
≥ 1.90 m^2 | 50 mg twice daily

Table 2 Recommended Dosage: KOSELUGO Oral Granules
Body Surface Area [The recommended dosage of KOSELUGO oral granules for patients with a BSA less than 0.40 m^2 has not been established.] | KOSELUGO Oral Granules
0.40 – 0.59 m^2 | 12.5 mg twice daily
0.60 – 0.69 m^2 | 15 mg twice daily
0.70 – 0.89 m^2 | 20 mg twice daily
0.90 – 1.09 m^2 | 25 mg twice daily
1.10 – 1.29 m^2 | 30 mg twice daily
1.30 – 1.49 m^2 | 35 mg twice daily
1.50 – 1.69 m^2 | 40 mg twice daily
1.70 – 1.89 m^2 | 45 mg twice daily
≥ 1.90 m^2 | 50 mg twice daily

2.2 Administration

KOSELUGO is available in two dosage forms: KOSELUGO capsules and KOSELUGO oral granules. Prescribe KOSELUGO oral granules for patients who have difficulty swallowing whole capsules.

KOSELUGO Capsules

- Administer KOSELUGO capsules to patients who can swallow a whole capsule.
- Swallow KOSELUGO capsules whole. Do not open, chew or crush KOSELUGO capsules.
- KOSELUGO capsules may be administered with or without food.

KOSELUGO Oral Granules

Administer KOSELUGO oral granules to patients who have difficulty swallowing a whole capsule.

Sprinkle KOSELUGO oral granules on or mix with a small amount (about 1 to 3 teaspoons) of smooth yogurt, or fruit puree containing the following fruits: apple, banana, pear, or strawberry and consume within 30 minutes of preparation. If not consumed within 30 minutes of preparation, discard and prepare a new dose. If a dose has been partially consumed within 30 minutes of preparation, discard the remainder of the dose and do not prepare a new dose, aim to complete dosing within 30 minutes next time.

The KOSELUGO oral granules should be free-flowing. Do NOT use if the oral granules are clumped or stuck inside the capsule shell. Instruct the patient or caregiver to contact their pharmacy if this happens.

Discard the empty capsule shells after use.

Do NOT swallow, chew, or dissolve the capsule shells of KOSELUGO oral granules.

Do NOT chew or crush the KOSELUGO oral granules. Do NOT add oral granules to liquids.

Do NOT mix KOSELUGO oral granules in grapefruit or any juice, fruit puree or jam containing Seville orange.

Missed Dose

If a dose of KOSELUGO capsules or KOSELUGO oral granules is missed, make up that dose unless the next dose is due within 6 hours.

Vomiting

If vomiting occurs after taking a dose of KOSELUGO capsules or KOSELUGO oral granules, do not take an additional dose. Take the next dose at the regular scheduled time.

2.3 Dosage Modifications for Adverse Reactions

The recommended dose reductions for adverse reactions for KOSELUGO capsules and KOSELUGO oral granules are provided in Tables 3 and 4, respectively.

Table 3 Recommended Dose Reductions for KOSELUGO Capsules for Adverse Reactions
Body Surface Area | First Dose Reduction (mg/dose) |  | Second Dose Reduction (mg/dose)
Body Surface Area | Morning | Evening | Morning | Evening
0.55 – 0.69 m^2 | 10 | 10 | 10 mg once daily
0.70 – 0.89 m^2 | 20 | 10 | 10 | 10
0.90 – 1.09 m^2 | 25 | 10 | 10 | 10
1.10 – 1.29 m^2 | 25 | 20 | 20 | 10
1.30 – 1.49 m^2 | 25 | 25 | 25 | 10
1.50 – 1.69 m^2 | 30 | 30 | 25 | 20
1.70 – 1.89 m^2 | 35 | 30 | 25 | 20
≥ 1.90 m^2 | 35 | 35 | 25 | 25
Permanently discontinue KOSELUGO capsules in patients unable to tolerate two dose reductions.

Table 4 Recommended Dose Reductions for KOSELUGO Oral Granules for Adverse Reactions
Body Surface Area | First Dose Reduction (mg/dose) |  | Second Dose Reduction (mg/dose)
Body Surface Area | Morning | Evening | Morning | Evening
0.40 – 0.59 m^2 | 10 | 10 | 7.5 | 7.5
0.60 – 0.69 m^2 | 12.5 | 12.5 | 10 | 10
0.70 – 0.89 m^2 | 15 | 15 | 12.5 | 12.5
0.90 – 1.09 m^2 | 20 | 20 | 15 | 15
1.10 – 1.29 m^2 | 22.5 | 22.5 | 15 | 15
1.30 – 1.49 m^2 | 25 | 25 | 25 | 10
1.50 – 1.69 m^2 | 30 | 30 | 25 | 20
1.70 – 1.89 m^2 | 35 | 30 | 25 | 20
≥ 1.90 m^2 | 35 | 35 | 25 | 25
Permanently discontinue KOSELUGO oral granules in patients unable to tolerate two dose reductions.

The recommended dosage modifications of KOSELUGO capsules and KOSELUGO oral granules for adverse reactions are provided in Table 5.

Table 5 Recommended Dosage Modifications for Adverse Reactions
Severity of Adverse Reaction | Recommended Dosage Modifications for KOSELUGO capsules and KOSELUGO oral granules
Left Ventricular Dysfunction [see Warnings and Precautions (5.1)]
- Asymptomatic decrease in left ventricular ejection fraction (LVEF) of 10% or greater from baseline and less than lower level of normal | Withhold until resolution. Resume at reduced dose.
- Symptomatic decreased LVEF - Grade 3 or 4 decreased LVEF | Permanently discontinue.
Ocular Toxicity [see Warnings and Precautions (5.2)]
- Retinal Pigment Epithelial Detachment (RPED) | Withhold until resolution. Resume at reduced dose.
- Retinal vein occlusion (RVO) | Permanently discontinue.
Gastrointestinal Toxicity [see Warnings and Precautions (5.3)]
- Grade 3 Diarrhea | Withhold until improved to Grade 0 or 1. Resume at same dose. Permanently discontinue if no improvement within 3 days.
- Grade 4 Diarrhea | Permanently discontinue.
- Grade 3 or 4 Colitis | Permanently discontinue.
Skin Toxicity [see Warnings and Precautions (5.4)]
- Grade 3 or 4 | Withhold until improvement. Resume at reduced dose.
Increased Creatine Phosphokinase (CPK) [see Warnings and Precautions (5.5)]
- Grade 4 Increased CPK - Any Increased CPK and myalgia | Withhold until improved to Grade 0 or 1. Resume at reduced dose. Permanently discontinue if no improvement within 3 weeks.
- Rhabdomyolysis | Permanently discontinue.
Other Adverse Reactions [see Adverse Reactions (6.1)]
- Intolerable Grade 2 - Grade 3 | Withhold KOSELUGO until improved to Grade 0 or 1. Resume at reduced dose.
- Grade 4 | Withhold KOSELUGO until improved to Grade 0 or 1. Resume at reduced dose. Consider discontinuation.

* Per National Cancer Institute Common Terminology Criteria for Adverse Events version 4.03.

2.4 Recommended Dosage in Patients with Hepatic Impairment

Severe Hepatic Impairment

The recommended dosage of KOSELUGO for use in patients with severe hepatic impairment (Child-Pugh C) has not been established [see Use in Specific Populations (8.6)].

Moderate Hepatic Impairment

The recommended dosage of KOSELUGO capsules (see Table 6) and KOSELUGO oral granules (see Table 7) for pediatric patients 1 year of age or older with moderate hepatic impairment (Child-Pugh B) is based on body surface area; 20 mg/m^2 orally twice daily, until disease progression or unacceptable toxicity [see Dosage and Administration (2.2)].

Table 6 Recommended Dosage of KOSELUGO Capsules for Moderate Hepatic Impairment
Body Surface Area | Moderate Hepatic Impairment (Child-Pugh B) (mg/dose)
Body Surface Area | Morning | Evening
0.55 – 0.69 m^2 | 10 | 10
0.70 – 0.89 m^2 | 20 | 10
0.90 – 1.09 m^2 | 20 | 20
1.10 – 1.29 m^2 | 25 | 25
1.30 – 1.49 m^2 | 30 | 25
1.50 – 1.69 m^2 | 35 | 30
1.70 – 1.89 m^2 | 35 | 35
≥ 1.90 m^2 | 40 | 40

Table 7 Recommended Dosage of KOSELUGO Oral Granules for Moderate Hepatic Impairment
Body Surface Area | Moderate Hepatic Impairment (Child‑Pugh B) (mg/dose)
Body Surface Area | Morning | Evening
0.40 – 0.59 m^2 | 10 | 10
0.60 – 0.69 m^2 | 12.5 | 12.5
0.70 – 0.89 m^2 | 15 | 15
0.90 – 1.09 m^2 | 20 | 20
1.10 – 1.29 m^2 | 25 | 25
1.30 – 1.49 m^2 | 30 | 25
1.50 – 1.69 m^2 | 35 | 30
1.70 – 1.89 m^2 | 35 | 35
≥ 1.90 m^2 | 40 | 40

2.5 Dosage Modifications for Drug Interactions

Strong or Moderate CYP3A4 Inhibitors or Fluconazole

Avoid coadministration of strong or moderate CYP3A4 inhibitors or fluconazole with KOSELUGO. If coadministration with strong or moderate CYP3A4 inhibitors or fluconazole cannot be avoided, reduce the KOSELUGO dosage as recommended in Table 8 (KOSELUGO capsules) and Table 9 (KOSELUGO oral granules). After discontinuation of the strong or moderate CYP3A4 inhibitor or fluconazole for 3-elimination half-lives, resume the KOSELUGO dose that was taken prior to initiating the inhibitor or fluconazole [see Drug Interactions (7.1)].

Table 8 Recommended Dosage of KOSELUGO Capsules for Coadministration with Strong or Moderate CYP3A4 Inhibitors or Fluconazole
Body Surface Area | If the current dosage is 25 mg/m^2 twice daily, reduce to 20 mg/m^2 twice daily (mg/dose) |  | If the current dosage is 20 mg/m^2 twice daily, reduce to 15 mg/m^2 twice daily (mg/dose)
Body Surface Area | Morning | Evening | Morning | Evening
0.55 – 0.69 m^2 | 10 | 10 | 10 mg once daily
0.70 – 0.89 m^2 | 20 | 10 | 10 | 10
0.90 – 1.09 m^2 | 20 | 20 | 20 | 10
1.10 – 1.29 m^2 | 25 | 25 | 25 | 10
1.30 – 1.49 m^2 | 30 | 25 | 25 | 20
1.50 – 1.69 m^2 | 35 | 30 | 25 | 25
1.70 – 1.89 m^2 | 35 | 35 | 30 | 25
≥ 1.90 m^2 | 40 | 40 | 30 | 30

Table 9 Recommended Dosage of KOSELUGO Oral Granules for Coadministration with Strong or Moderate CYP3A4 Inhibitors or Fluconazole
Body Surface Area | If the current dosage is 25 mg/m^2 twice daily, reduce to 20 mg/m^2 twice daily (mg/dose) |  | If the current dosage is 20 mg/m^2 twice daily, reduce to 15 mg/m^2 twice daily (mg/dose)
Body Surface Area | Morning | Evening | Morning | Evening
0.40 – 0.59 m^2 | 10 | 10 | 7.5 | 7.5
0.60 – 0.69 m^2 | 12.5 | 12.5 | 10 | 7.5
0.70 – 0.89 m^2 | 15 | 15 | 10 | 10
0.90 – 1.09 m^2 | 20 | 20 | 15 | 15
1.10 – 1.29 m^2 | 25 | 25 | 25 | 10
1.30 – 1.49 m^2 | 30 | 25 | 25 | 20
1.50 – 1.69 m^2 | 35 | 30 | 25 | 25
1.70 – 1.89 m^2 | 35 | 35 | 30 | 25
≥ 1.90 m^2 | 40 | 40 | 30 | 30

3 DOSAGE FORMS AND STRENGTHS

Capsules:

- 10 mg selumetinib: white to off-white, opaque, hard capsule sealed with a clear band and marked with “SEL 10” in black ink.
- 25 mg selumetinib: blue, opaque, hard capsule sealed with a clear band and marked with “SEL 25” in black ink.

Oral Granules:

- 5 mg selumetinib: off-white to light-yellow free-flowing oral granules contained within capsules. The capsules have a yellow cap and white body. The cap is printed with “sel 5” in black ink, and body is printed with a sprinkle capsule image indicating opening.
- 7.5 mg selumetinib: off-white to light-yellow free-flowing oral granules contained within capsules. The capsules have a pink cap and white body. The cap is printed with “sel 7.5” in black ink, and body is printed with a sprinkle capsule image indicating opening.

4 CONTRAINDICATIONS

None.

5 WARNINGS AND PRECAUTIONS

5.1 Left Ventricular Dysfunction

KOSELUGO can cause cardiomyopathy, defined as a decrease in left ventricular ejection fraction (LVEF) ≥ 10% below baseline. KOSELUGO has not been studied in patients with a history of clinically significant cardiac disease or LVEF less than 55% prior to treatment.

Pediatric patients

In the NF1 PN pediatric safety pool (N = 134) [see Adverse Reactions (6.1)], Grade 2 LVEF decrease [Grade 2 LVEF decrease (40% to 50%; 10 to 19% drop from baseline)], based on reported adverse reactions, occurred in 17% of evaluable patients. Decreased LVEF of ≥ 20% occurred in 0.7% of patients and resulted in dose interruption and dose reduction. Decreased LVEF resolved in 75% of these patients. The median time to first occurrence of LVEF decrease was approximately 12 months (median duration approximately 3 months).

Adult Patients

In the KOMET adult NF1 PN study (N = 71) [see Adverse Reactions (6.1)], Grade 2 LVEF decrease [Grade 2 LVEF decrease (40% to 50%; 10 to 19% drop from baseline)], based on echocardiogram results, occurred in 14% of evaluable patients. Decreased LVEF resulted in dose interruption in 1.4% of patients. The median time to first occurrence of LVEF decrease was approximately 4 months (median duration approximately 4 months).

Assess ejection fraction by echocardiogram prior to initiating treatment, every 3 months during the first year of treatment, every 6 months thereafter, and as clinically indicated. Withhold, reduce dose, or permanently discontinue KOSELUGO based on severity of adverse reaction [see Dosage and Administration (2.3)]. In patients who interrupt KOSELUGO for decreased LVEF, obtain an echocardiogram or a cardiac MRI every 3 to 6 weeks until resolution. Upon resolution of decreased LVEF to greater than or equal to the institutional LLN, obtain an echocardiogram or a cardiac MRI every 2 to 3 months or as directed by the cardiologist.

5.2 Ocular Toxicity

KOSELUGO can cause ocular toxicity, including retinal vein occlusion (RVO), retinal pigment epithelial detachment (RPED), and blurred vision.

Pediatric Patients

In the NF1 PN pediatric safety pool (N = 134) [see Adverse Reactions (6.1)], blurred vision, photophobia, cataracts, ocular hypertension, and retinal tear occurred in 13% of pediatric patients receiving KOSELUGO. Blurred vision resulted in dose interruption in 1.5% of patients. Ocular toxicity resolved in 76% of these patients. RPED occurred in the pediatric population during treatment with single agent KOSELUGO and resulted in permanent discontinuation.

Adult Patients

In the KOMET adult NF1 PN study (N = 71) [see Adverse Reactions (6.1)], blurred vision and vitreous floaters occurred in 6% of patients receiving KOSELUGO. Serious ocular toxicities including RVO and RPED, occurred in an unapproved population of adult patients with multiple tumor types who received KOSELUGO as a single agent or in combination with other anti-cancer agents.

Conduct comprehensive ophthalmic assessments prior to initiating KOSELUGO, at regular intervals during treatment, and for new or worsening visual changes. Permanently discontinue KOSELUGO in patients with RVO. Withhold KOSELUGO in patients with RPED, follow up with optical coherence tomography assessments every 3 weeks until resolution, and resume KOSELUGO at a reduced dose. For other ocular toxicities, withhold, reduce dose, or permanently discontinue KOSELUGO based on severity of the adverse reaction [see Dosage and Administration (2.3)].

5.3 Gastrointestinal Toxicity

KOSELUGO can cause gastrointestinal toxicities, including diarrhea and colitis.

Pediatric Patients

In the NF1 PN pediatric safety pool (N = 134) [see Adverse Reactions (6.1)], diarrhea occurred in 59% of patients who received KOSELUGO, including Grade 3 in 10% of patients. Diarrhea resulting in permanent discontinuation occurred in 0.7% of patients. Diarrhea resulting in dose interruption occurred in 10% of patients. The median time to first onset of diarrhea was approximately 2 months and the median duration was 5 days. Colitis occurred in an unapproved population of pediatric patients with multiple tumor types who received KOSELUGO as a single agent.

Adult Patients

In the KOMET adult NF1 PN study (N = 71) [see Adverse Reactions (6.1)], diarrhea occurred in 42% patients who received KOSELUGO. Diarrhea resulting in dose interruption occurred in 1.4% of patients. The median time to first onset of diarrhea was approximately 1 month and the median duration was 7 days. Serious gastrointestinal toxicities, including perforation, colitis, ileus, and intestinal obstruction, occurred in an unapproved population of adult patients with multiple tumor types who received KOSELUGO as a single agent or in combination with other anti-cancer agents.

Advise patients to start an anti-diarrheal agent (e.g., loperamide) immediately after the first episode of unformed, loose stool and to increase fluid intake during diarrhea episodes. Withhold, reduce dose, or permanently discontinue KOSELUGO based on severity of adverse reaction [see Dosage and Administration (2.3)].

5.4 Skin Toxicity

KOSELUGO can cause severe rashes, including dermatitis acneiform.

Pediatric Patients

In the NF1 PN pediatric safety pool (N = 134) [see Adverse Reactions (6.1)], rash occurred in 68% of patients who received KOSELUGO. The most frequent rashes included dermatitis acneiform (47%) and maculopapular rash (31%). Pruritus (30%), alopecia (26%), and eczema (24%) occurred in patients who received KOSELUGO. Grade 3 rash occurred in 5% of patients. Rash resulted in dose interruption in 8% of patients and dose reduction in 3.7% of patients.

Adult Patients

In the KOMET adult NF1 PN study (N = 71) [see Adverse Reactions (6.1)], rash occurred in 85% of patients who received KOSELUGO. The most frequent rash included dermatitis acneiform (66%). Alopecia (18%) and pruritus (10%) occurred in patients who received KOSELUGO. Grade 3 rash occurred in 4.2% of patients. Rash resulted in dose interruption in 2.8% of patients, dose reduction in 2.8% of patients, and permanent discontinuation in 2.8% of patients.

Other skin toxicities, including severe palmar-plantar erythrodysesthesia syndrome, occurred in an unapproved population of adult patients with multiple tumor types who received KOSELUGO as a single agent or in combination with other anti-cancer agents.

Monitor for severe skin rashes. Withhold, reduce dose, or permanently discontinue KOSELUGO based on severity of adverse reaction [see Dosage and Administration (2.3)].

5.5 Increased Creatine Phosphokinase

KOSELUGO can cause increased creatine phosphokinase (CPK), myalgia, and rhabdomyolysis.

Pediatric Patients

In the NF1 PN pediatric safety pool (N = 134) [see Adverse Reactions (6.1)], increased creatine phosphokinase (CPK), based on laboratory data, occurred in 73% of patients who received KOSELUGO, including Grade 3 or 4 in 8% of patients. Increased CPK resulted in dose interruption and dose reduction in 4% of patients. Increased CPK concurrent with myalgia occurred in 5% of patients, including one patient who permanently discontinued KOSELUGO for myalgia.

Adults

In the KOMET adult NF1 PN study (N = 71) [see Adverse Reactions (6.1)], increased creatine phosphokinase (CPK), based on laboratory data, occurred in 70% of patients who received KOSELUGO, including Grade 3 or 4 in 7% of patients. Increased CPK resulted in dose interruption and dose reduction in 4.2% and 2.8% of patients, respectively. Increased CPK concurrent with myalgia occurred in 1.4% of patients. Rhabdomyolysis occurred in an unapproved adult population who received KOSELUGO as a single agent.

Obtain serum CPK prior to initiating KOSELUGO, periodically during treatment, and as clinically indicated. If increased CPK occurs, evaluate patients for rhabdomyolysis or other causes. Withhold, reduce dose, or permanently discontinue KOSELUGO based on severity of adverse reaction [see Dosage and Administration (2.3)].

5.6 Increased Levels of Vitamin E and Increased Risk of Bleeding (KOSELUGO Capsules)

KOSELUGO capsules can cause increased levels of vitamin E and increased risk of bleeding.

KOSELUGO capsules contain vitamin E (10 mg capsules contain 32 mg vitamin E as the excipient, D-alpha-tocopheryl polyethylene glycol 1000 succinate (TPGS); while KOSELUGO 25 mg capsules contain 36 mg vitamin E as TPGS). Vitamin E can inhibit platelet aggregation and antagonize vitamin K-dependent clotting factors. Daily vitamin E intake that exceeds the recommended or safe limits may increase the risk of bleeding. Supplemental vitamin E is not recommended if daily vitamin E intake (including the amount of vitamin E in KOSELUGO and supplement) will exceed the recommended or safe limits.

An increased risk of bleeding in patients may occur in patients who are co-administered vitamin K antagonists or anti-platelet antagonists with KOSELUGO capsules. Monitor for bleeding in these patients. Increase international normalized ratio (INR) monitoring, as appropriate, in patients taking a vitamin K antagonist. Perform anticoagulant assessments, including INR or prothrombin time, more frequently and adjust the dose of vitamin K antagonists or anti-platelet agents as appropriate.

KOSELUGO oral granules do not contain vitamin E [see Drug Interactions (7.1)].

5.7 Embryo-Fetal Toxicity

Based on findings from clinical trials, animal studies and its mechanism of action, KOSELUGO can cause fetal harm when administered to a pregnant woman. In KOMET, a first trimester spontaneous abortion was reported in a patient receiving KOSELUGO.

In animal reproduction studies, administration of selumetinib to mice during organogenesis caused reduced fetal weight, adverse structural defects, and effects on embryo fetal survival at approximate exposures > 5 times the human exposure at the clinical dose of 25 mg/m^2 twice daily. Advise pregnant women of the potential risk to a fetus. Advise females of reproductive potential to use effective contraception during treatment with KOSELUGO and for 1 week after the last dose. Advise males with female partners of reproductive potential to use effective contraception during treatment with KOSELUGO and for 1 week after the last dose [see Use in Specific Populations (8.1, 8.3)].

6 ADVERSE REACTIONS

The following clinically significant adverse reactions are described elsewhere in the labeling:

- Left Ventricular Dysfunction [see Warnings and Precautions (5.1)]
- Ocular Toxicity [see Warnings and Precautions (5.2)]
- Gastrointestinal Toxicity [see Warnings and Precautions (5.3)]
- Skin Toxicity [see Warnings and Precautions (5.4)]
- Increased Creatine Phosphokinase [see Warnings and Precautions (5.5)]

6.1 Clinical Trials Experience

Because clinical trials are conducted under widely varying conditions, adverse reaction rates observed in the clinical trials of a drug cannot be directly compared to rates in the clinical trials of another drug and may not reflect the rates observed in practice.

The NF1 PN pediatric safety pool described in the WARNINGS AND PRECAUTIONS reflects exposure to KOSELUGO at the recommended dosage in 134 pediatric patients in SPRINKLE (N = 36) (NCT05309668), SPRINT Phase I (N = 24) (NCT01362803), SPRINT Phase II Stratum 1 (N = 50) [see Clinical Studies (14.1)], and Phase I Food Effect Study (N = 24) (NCT05101148). Among pediatric patients, the duration of KOSELUGO exposure was 12 months or longer (80%), more than 2 years (44%), or more than 3 years (37%). The most common adverse reactions in pediatric patients (≥ 40%) are vomiting, diarrhea, increased creatine phosphokinase, dry skin, paronychia, nausea, dermatitis acneiform, and pyrexia.

In the KOMET adult NF1 PN study, 71 adult patients received KOSELUGO at the recommended dosage [see Clinical Studies (14.1)]. Among adult patients, the duration of KOSELUGO exposure in the randomized period was 6 months or longer (92%), and 11 months or longer (66%). The most common adverse reactions in adult patients (≥ 40%) are rash (all), dermatitis acneiform, and diarrhea.

Neurofibromatosis Type 1 (NF1) with Inoperable Plexiform Neurofibromas (PN)

Pediatrics 2-18 years of Age (SPRINT Phase II Stratum 1)

The safety of KOSELUGO was evaluated in SPRINT Phase II Stratum 1 [see Clinical Studies (14.1)]. Eligible patients were 2-18 years of age with neurofibromatosis type 1 (NF1) who had inoperable plexiform neurofibromas (PN) that was causing significant morbidity. Patients were excluded for abnormal LVEF, uncontrolled hypertension (blood pressure ≥ the 95th percentile for age, height, and sex), any current or past history of RVO or RPED, intraocular pressure > 21 mmHg (or upper limit of normal adjusted by age), uncontrolled glaucoma, and inability to swallow whole capsules. Patients received KOSELUGO 25 mg/m^2 orally twice daily (N = 50). Among these patients, 88% were exposed for 12 months or longer and 66% were exposed for greater than 2 years.

Serious adverse reactions occurred in 24% of patients who received KOSELUGO. Serious adverse reactions that occurred in 2 or more patients were anemia, hypoxia and diarrhea.

Permanent discontinuation due to an adverse reaction occurred in 12% of patients who received KOSELUGO. Adverse reactions resulting in permanent discontinuation of KOSELUGO included increased blood creatinine, increased weight, diarrhea, paronychia, malignant peripheral nerve sheath tumor, acute kidney injury, and skin ulcer.

Dosage interruptions and dose reductions due to adverse reactions occurred in 80% and 24% of patients who received KOSELUGO, respectively. Adverse reactions requiring a dosage interruption or reduction in ≥ 5% of patients were vomiting, paronychia, diarrhea, nausea, abdominal pain, rash, skin infection, influenza-like illness, pyrexia and weight gain.

The most common adverse reactions (≥ 40%) were vomiting, rash (all), abdominal pain, diarrhea, nausea, dry skin, fatigue, musculoskeletal pain, pyrexia, acneiform rash, stomatitis, headache, paronychia, and pruritus.

Table 10 presents the adverse reactions in SPRINT Phase II Stratum 1.

Table 10 Adverse Reactions (≥ 20%) in Patients Who Received KOSELUGO in SPRINT Phase II Stratum 1
Adverse Reaction | KOSELUGO; (N = 50)
Adverse Reaction | All Grades; (%) | Grade ≥ 3; (%)*
Gastrointestinal
Vomiting | 82 | 6
Abdominal pain [Abdominal pain includes abdominal pain; abdominal pain upper] | 76 | 0
Diarrhea | 70 | 16
Nausea | 66 | 2
Stomatitis [Stomatitis includes stomatitis; mouth ulceration] | 50 | 0
Constipation | 34 | 0
Skin and Subcutaneous Tissue
Rash (all) [Rash (all) includes dermatitis acneiform; rash maculo-papular; erythema; rash pustular; rash; urticaria; exfoliative rash; rash pruritic; rash erythematous] | 80 | 6
Dry skin | 60 | 0
Rash acneiform [Rash (acneiform) includes dermatitis acneiform] | 50 | 4
Paronychia [Paronychia includes paronychia; nail infection] | 48 | 6
Pruritus | 46 | 0
Dermatitis [Dermatitis includes dermatitis; dermatitis atopic; dermatitis diaper; eczema; seborrheic dermatitis; skin irritation] | 36 | 4
Hair changes [Hair changes include alopecia; hair color change] | 32 | 0
Musculoskeletal and Connective Tissue
Musculoskeletal pain [Musculoskeletal pain includes pain in extremity; back pain; neck pain; musculoskeletal pain] | 58 | 0
General
Fatigue [Fatigue includes fatigue; malaise] | 56 | 0
Pyrexia | 56 | 8
Edema [Edema includes peripheral swelling; edema; localized edema] | 20 | 0
Nervous System
Headache | 48 | 2
Respiratory, Thoracic and Mediastinal
Epistaxis | 28 | 0
Renal and Urinary System
Hematuria | 22 | 2
Proteinuria | 22 | 0
Metabolism and Nutrition
Decreased appetite | 22 | 0
Cardiac System
Decreased ejection fraction | 22 | 0
Sinus tachycardia | 20 | 0
Infections
Skin infection [Skin infection includes skin infection; abscess; cellulitis; impetigo; staphylococcal skin infection] | 20 | 2
* All events were Grade 3.

Clinically relevant adverse reactions that occurred < 20% of patients include:

- Eye: visual impairment.
- Gastrointestinal Disorders: dry mouth.
- General Disorders: facial edema, including periorbital edema and face edema.
- Metabolism and Nutrition: increased weigh.t
- Renal and Urinary System: acute kidney injury.
- Respiratory, Thoracic & Mediastinal: dyspnea, including exertional dyspnea and dyspnea at rest.
- Vascular: hypertension.

Table 11 presents the laboratory abnormalities in SPRINT Phase II Stratum 1.

Table 11 Select Laboratory Abnormalities (≥ 15%) Worsening from Baseline in Patients Who Received KOSELUGO in SPRINT Phase II Stratum 1
Laboratory Abnormality | KOSELUGO
Laboratory Abnormality | All Grades (%) [The denominator used to calculate the rate varied from 39 to 49 based on the number of patients with a baseline value and at least one post-treatment value.] | Grade ≥ 3 (%)
Chemistry
Increased creatine phosphokinase (CPK) | 79 | 7 [Includes one Grade 4 increased CPK and one Grade 4 increased potassium.]
Decreased albumin | 51 | 0
Increased aspartate aminotransferase (AST) | 41 | 2
Increased alanine aminotransferase (ALT) | 35 | 4
Increased lipase | 32 | 5
Increased potassium | 27 | 4
Decreased potassium | 18 | 2§
Increased alkaline phosphatase | 18 | 0
Increased amylase | 18 | 0
Increased sodium | 18 | 0
Decreased sodium | 16 | 0
Hematology
Decreased hemoglobin | 41 | 4
Decreased neutrophils | 33 | 4
Decreased lymphocytes | 20 | 2

Adults ≥ 18 years of Age (KOMET)

The safety of KOSELUGO was evaluated in KOMET [see Clinical Studies (14.1)]. Eligible patients were 18 years of age or older with NF1 who had symptomatic, inoperable PN. Patients were excluded for abnormal LVEF, uncontrolled hypertension, any current or past history of RVO or RPED/CSR, intraocular pressure > 21 mmHg (or upper limit of normal adjusted by age), uncontrolled glaucoma, and inability to swallow whole capsules. Among the patients (N = 137) who have received KOSELUGO, the median duration of KOSELUGO treatment was 11 months with a range of 10 days to 31 months.

Serious adverse reactions occurred in 14% of patients who received KOSELUGO. Serious adverse reactions occurring in more than one patient included cellulitis (2.8%).

Permanent discontinuation due to an adverse reaction occurred in 13% of patients who received KOSELUGO. Adverse reactions resulting in permanent discontinuation of KOSELUGO included dermatitis acneiform, cellulitis, nausea, wound, neurofibrosarcoma, neurofibrosarcoma recurrent, psychiatric decompensation, ulcerative keratitis, and nail disorder.

Dosage interruptions and dose reductions due to adverse reactions occurred in 27% and 14% of patients who received KOSELUGO, respectively. Adverse reactions requiring a dosage reduction in 2 or more patients were paronychia, increased CPK, increased ALT, increased AST, rash, and alopecia. Adverse reactions requiring a dosage interruption in 2 or more patients were increased CPK, rash, headache, abdominal pain, nausea, and COVID‑19.

The most common adverse reactions (≥ 40%) were rash (all), rash (acneiform), and diarrhea.

Table 12 presents the adverse reactions in the KOMET study. The 12 cycle (48 weeks) randomization period for KOSELUGO versus placebo was followed by a single arm treatment period where all patients received KOSELUGO (placebo patients crossed over to KOSELUGO at end of the randomized period). No new adverse reactions were identified during the open-label period.

Table 12 Adverse Reactions (≥ 20%) in Patients Who Received KOSELUGO Compared with Placebo in KOMET
Adverse Reactions | Randomized to KOSELUGO* (N = 71) |  | Randomized to Placebo* (N = 74)
Adverse Reactions | All Grades (%) | Grades ≥ 3 (%) | All Grades (%) | Grades ≥ 3 (%)
Skin and Subcutaneous Tissue
Rash (all) [Rash (all): acne, dermatitis, dermatitis acneiform, erythema, exfoliative rash, rash, rash erythematous, rash follicular, rash maculo-papular, rash pruritic, rash pustular, urticaria, rash macular, and rash papular.] | 85 | 4.2 | 23 | 0
Rash acneiform [Rash acneiform: acne and dermatitis acneiform] | 66 | 2.8 | 11 | 0
Musculoskeletal and Connective Tissue
Musculoskeletal pain [Musculoskeletal pain: arthralgia, back pain, musculoskeletal chest pain, musculoskeletal discomfort, musculoskeletal pain, musculoskeletal stiffness, myalgia, neck pain, non-cardiac chest pain, and pain in extremity.] | 23 | 0 | 22 | 0
Gastrointestinal
Diarrhea | 42 | 0 | 12 | 0
Vomiting | 25 | 0 | 8 | 0
Nausea | 25 | 0 | 16 | 0
General
Edema [Edema: localized edema, edema, edema peripheral, and peripheral swelling.] | 21 | 0 | 1.4 | 0
Fatigue [Fatigue: asthenia and fatigue.] | 24 | 0 | 14 | 0
* ADRs of patients during the 12 Cycle (48 weeks) randomization period.

Clinically relevant adverse reactions in < 20% of patients who received KOSELUGO versus placebo based on reported adverse reactions included hair changes (18% vs 11%), paronychia (13% vs 4%), pyrexia (7% vs 4%), stomatitis (18% vs 5%), and skin infection (6% vs 1%), respectively. Decreased ejection fraction in patients who received KOSELUGO versus placebo based on reported echocardiogram results occurred in 14% and 11% of patients, respectively.

Table 13 presents the laboratory abnormalities in the KOMET study.

Table 13 Select Laboratory Abnormalities (≥ 15%) That Worsened from Baseline in Patients Who Received KOSELUGO with a Difference Between Arms of > 10% Compared to Placebo in KOMET
Laboratory Abnormalities | Randomized to; KOSELUGO*; (N = 71) |  | Randomized to; Placebo*; (N = 74)
Laboratory Abnormalities | All Grades; (%) | Grades ≥ 3; (%) | All Grades; (%) | Grades ≥ 3; (%)
Chemistry
Increase creatine phosphokinase | 70 | 7 | 15 | 1.4
Increased aspartate aminotransferase (AST) | 48 | 2.9 | 12 | 0
Increased alanine aminotransferase (ALT) | 39 | 4.3 | 14 | 0
Decreased albumin | 24 | 1.4 | 6 | 0
Increased alkaline phosphatase | 17 | 1.4 | 7 | 0
Increased amylase | 17 | 1.4 | 5 | 0
Decreased magnesium | 16 | 0 | 5 | 0
Hematology
Decreased hemoglobin | 24 | 0 | 14 | 0
* Lab abnormalities of patients during the 12 Cycle (48 weeks) randomization period.

Pediatrics > 1 year of Age on KOSELUGO Granules (SPRINKLE)

The safety of KOSELUGO oral granules was evaluated in SPRINKLE (NCT05309668), a dose-finding and activity estimating, single-arm, multicenter study in 36 pediatric patients ages 1 year to less than 7 years with a clinical diagnosis of NF1- related symptomatic, inoperable PN. The study evaluated the pharmacokinetics (PK), safety, efficacy, and tolerability of KOSELUGO oral granules. Study patients were to receive KOSELUGO oral granules for 25 cycles at a dose equivalent to 25 mg/m^2 BSA twice daily until disease progression or unacceptable toxicity. The median age was approximately 4 years (range: 1 to 7 years), 61% were male, 61% were White, 14% were Asian and 3% were Black or African American.

In the SPRINKLE study, the median duration of KOSELUGO oral granules treatment in pediatric patients with neurofibromatosis type 1 (NF1) plexiform neurofibromas (PN) was 11 months (range: 3-25 months). Serious adverse reactions occurred in 6% of patients who received KOSELUGO oral granules. Serious adverse reactions occurred in 1 patient each and included pyrexia, gastroenteritis and upper respiratory infection. A total of 31% of patients had an adverse reaction leading to a dosage interruption. Adverse reactions requiring a dosage interruption in ≥ 5% of patients were pyrexia, vomiting, diarrhea, upper respiratory infection, gastroenteritis and eczema. The most common adverse reactions (≥ 40%) were pyrexia, dry skin, and paronychia.

The observed safety profile of KOSELUGO oral granules in the SPRINKLE study was consistent with the known safety profile of KOSELUGO capsules.

7 DRUG INTERACTIONS

7.1 Effect of Other Drugs on KOSELUGO

Strong or Moderate CYP3A4 Inhibitors or Fluconazole
Management | - Avoid concomitant use of strong or moderate CYP3A4 inhibitors or fluconazole with KOSELUGO. If coadministration with strong or moderate CYP3A4 inhibitors or fluconazole cannot be avoided, reduce KOSELUGO dosage [see Dosage and Administration (2.4)].
Clinical Impact | - Concomitant use of KOSELUGO with a strong or moderate CYP3A4 inhibitor or fluconazole increased selumetinib plasma concentrations [see Clinical Pharmacology (12.3)], which may increase the risk of adverse reactions.
Strong or Moderate CYP3A4 Inducers
Management | - Avoid concomitant use of strong or moderate CYP3A4 inducers with KOSELUGO.
Clinical Impact | - Concomitant use of KOSELUGO with a strong or moderate CYP3A4 inducer decreased selumetinib plasma concentrations [see Clinical Pharmacology (12.3)], which may reduce KOSELUGO efficacy.
Vitamin E
Management | - Supplemental vitamin E is not recommended if daily vitamin E intake (including the amount of vitamin E in KOSELUGO capsules and supplement) will exceed the recommended or safe limits. - Monitor for bleeding in patients administered a vitamin‑K antagonist or an anti‑platelet agent with KOSELUGO capsules. Increase INR monitoring, as appropriate, in patients taking a vitamin‑K antagonist [see Warnings and Precautions (5.3)].
Clinical Impact | - KOSELUGO capsules contain vitamin E and daily vitamin E intake that exceeds the recommended or safe limits may increase the risk of bleeding. An increased risk of bleeding may occur in patients taking a vitamin‑K antagonist or an anti‑platelet agent with KOSELUGO capsules.

8 USE IN SPECIFIC POPULATIONS

8.1 Pregnancy

Risk Summary

Based on findings from animal studies and its mechanism of action [see Clinical Pharmacology (12.1)], KOSELUGO can cause fetal harm when administered to a pregnant woman. There are no available data on the use of KOSELUGO in pregnant women to evaluate drug-associated risk. In animal reproduction studies, administration of selumetinib to mice during organogenesis caused reduced fetal weight, adverse structural defects, and effects on embryofetal survival at exposures approximately > 5 times the human exposure at the clinical dose of 25 mg/m^2 twice daily (see Data). Advise pregnant women of the potential risk to the fetus.

In the U.S. general population, the estimated background risk of major birth defects and miscarriage in clinically recognized pregnancies is 2% to 4% and 15% to 20%, respectively.

Data

Human Data

In KOMET, a first trimester spontaneous abortion was reported in a patient receiving KOSELUGO.

Animal Data

In embryo-fetal development studies in mice at doses > 2.5 mg/kg twice daily (~5-times the human exposure based on area under the curve [AUC] at the clinical dose of 25 mg/m^2 twice daily), selumetinib caused increases in post-implantation loss, a reduction in mean fetal and litter weights, and an increased occurrence of open eye and cleft palate, but did not induce significant maternal toxicity.

Administration of selumetinib to pregnant mice from gestation Day 6 through lactation Day 20 resulted in reduced pup body weights and fewer pups met the pupil constriction criterion on day 21 post-partum. The incidence of malformations (e.g., prematurely open eye(s) and cleft palate) was increased even at the lowest dose of 0.5 mg/kg twice daily (maternal maximal concentration [Cmax] of ~0.6 times the human Cmax at the clinical dose of 25 mg/m^2 twice daily).

8.2 Lactation

Risk Summary

There are no data on the presence of selumetinib or its active metabolite in human milk or their effects on the breastfed child or milk production. Selumetinib and its active metabolite were present in the milk of lactating mice (see Data). Due to the potential for adverse reactions in a breastfed child, advise women not to breastfeed during treatment with KOSELUGO and for 1 week after the last dose.

Data

Animal Data

Selumetinib and its active metabolite were present in milk from mice dosed with selumetinib throughout gestation and lactation, with a mean plasma/milk ratio of 1.5 in lactating dams dosed at 5 mg/kg twice daily. Administration of selumetinib to dams during gestation and early lactation was associated with adverse events in pups, including reduced growth rates and incidence of malformations [see Use in Specific Populations (8.1)].

8.3 Females and Males of Reproductive Potential

KOSELUGO can cause fetal harm when administered to a pregnant woman [see Use in Specific Populations (8.1)].

Pregnancy Testing

Verify the pregnancy status of females of reproductive potential prior to initiating KOSELUGO [see Use in Specific Populations (8.1)].

Contraception

Females

Advise females of reproductive potential to use effective contraception during treatment and for 1 week after the last dose.

Males

Advise male patients with female partners of reproductive potential to use effective contraception during treatment with KOSELUGO and for 1 week after the last dose.

8.4 Pediatric Use

The safety and effectiveness have been established in pediatric patients 1 year of age and older with NF1 who have inoperable PN and the information on this use is discussed throughout the labeling. The safety and effectiveness of KOSELUGO have not been established in pediatric patients younger than 1 year of age.

Animal Toxicity Data

In 3-month general toxicology studies, male rats receiving selumetinib at doses ≥ 10 mg/kg daily (~60-times the human exposure based on AUC at the clinical dose of 25 mg/m^2 twice daily) showed growth plate dysplasia.

8.5 Geriatric Use

Clinical studies of KOSELUGO did not include a sufficient number of patients aged 65 and over to determine whether they respond differently from younger patients.

8.6 Hepatic Impairment

Selumetinib exposures increased in patients with moderate or severe hepatic impairment [see Clinical Pharmacology (12.3)]. Reduce the dose of KOSELUGO for patients with moderate hepatic impairment (Child-Pugh B). A recommended dosage of KOSELUGO for use in patients with severe hepatic impairment (Child-Pugh C) has not been established [see Dosage and Administration (2.4)].

10 OVERDOSAGE

Dialysis is not effective as KOSELUGO is highly protein bound and is extensively metabolized.

11 DESCRIPTION

KOSELUGO contains selumetinib sulfate, a kinase inhibitor. The chemical name is 5-[(4-bromo-2-chlorophenyl)amino]-4-fluoro-6-[(2-hydroxyethoxy)carbamoyl]-1-methyl-1H-benzimidazol-3-ium hydrogen sulfate. The molecular formula for selumetinib sulfate is C17H17BrClFN4O7S and the relative molecular mass is 555.76 g/mol. Selumetinib sulfate has the following structural formula:

Selumetinib sulfate is a white to yellow monomorphic crystalline powder that exhibits a pH dependent solubility. Selumetinib sulfate is freely soluble at pH < 1.5, sparingly soluble in the pH range at 1.5 to 3 and slightly soluble at pH > 3. Selumetinib sulfate has two ionizable functions with pKa values of 2.8 and 8.4.

KOSELUGO (selumetinib) 10 mg capsules for oral use, contain 10 mg selumetinib (equivalent to 12.1 mg selumetinib sulfate) and the excipient, vitamin E polyethylene glycol succinate. The capsule shell contains carnauba wax, carrageenan, hypromellose, potassium chloride, purified water, and titanium dioxide. The capsule is imprinted with black ink that contains ammonium hydroxide, iron oxide black, propylene glycol, and shellac.

KOSELUGO (selumetinib) 25 mg capsules for oral use, contain 25 mg selumetinib (equivalent to 30.25 mg selumetinib sulfate) and the excipient, vitamin E polyethylene glycol succinate. The capsule shell contains carnauba wax and/or cornstarch, carrageenan, FD&C blue 2, ferric oxide yellow, hypromellose, potassium chloride, purified water, and titanium dioxide. The capsule is imprinted with black ink that contains carnauba wax, FD&C Blue 2 aluminum lake, ferric oxide red, ferric oxide yellow, glyceryl monooleate, and shellac.

KOSELUGO (selumetinib) 5 mg oral granules contain 5 mg selumetinib (equivalent to 6.05 mg selumetinib sulfate). The uncoated cores contain selumetinib sulfate, glyceryl dibehenate, and stearoyl polyoxylglycerides. The granule coating contains acetone, hypromellose acetate succinate, and stearic acid. The capsule shell contains ferric oxide yellow, hypromellose, and titanium dioxide. The capsule shell is imprinted with black ink that contains butyl alcohol, dehydrated alcohol, ferric oxide black, isopropyl alcohol, potassium hydroxide, propylene glycol, purified water, shellac, and strong ammonia solution.

KOSELUGO (selumetinib) 7.5 mg oral granules contain 7.5 mg selumetinib (equivalent to 9.08 mg selumetinib sulfate). The uncoated cores contain selumetinib sulfate, glyceryl dibehenate, and stearoyl polyoxylglycerides. The granule coating contains acetone, hypromellose acetate succinate, and stearic acid. The capsule shell contains ferric oxide red, hypromellose, and titanium dioxide. The capsule shell is imprinted with black ink that contains butyl alcohol, dehydrated alcohol, ferric oxide black, isopropyl alcohol, potassium hydroxide, propylene glycol, purified water, shellac, and strong ammonia solution.

12 CLINICAL PHARMACOLOGY

12.1 Mechanism of Action

Selumetinib is an inhibitor of mitogen-activated protein kinase kinases 1 and 2 (MEK1/2). MEK1/2 proteins are upstream regulators of the extracellular signal-related kinase (ERK) pathway. Both MEK and ERK are critical components of the RAS-regulated RAF-MEK-ERK pathway, which is often activated in different types of cancers.

In genetically modified mouse models of NF1 that generate neurofibromas that recapitulate the genotype and phenotype of human NF1, oral dosing of selumetinib inhibited ERK phosphorylation, and reduced neurofibroma numbers, volume, and proliferation.

12.2 Pharmacodynamics

The exposure-response relationship and time course of pharmacodynamic response for the safety and effectiveness of KOSELUGO have not been fully characterized.

Cardiac Electrophysiology

At a dose 1.5-times the maximum recommended dose, clinically significant QTc interval prolongation was not observed.

12.3 Pharmacokinetics

Selumetinib pharmacokinetics were observed at steady state in adult and pediatric patients with NF1 and are presented as mean (CV%) unless otherwise indicated.

The maximum plasma concentration (Cmax) is 792 (49) ng/mL and systemic exposure (AUC) is 2141 (55) ng•h/mL following KOSELUGO 25 mg/m^2 twice daily. Selumetinib AUC and Cmax increases in a dose proportional manner over a dose range from 20 mg/m^2 to 30 mg/m^2 (0.8 to 1.2 times the recommended dose).

Selumetinib accumulation range is 1.2-1.5 fold following administration of KOSELUGO at 25 mg/m^2.

At the recommended dosage of 25 mg/m^2 of KOSELUGO oral granules (sprinkled on smooth yogurt, smooth fruit sauce, smooth fruit puree, or smooth fruit jam) twice daily in pediatric patients (> 1 year old to < 7 years old), the AUC0-24h following the first dose of KOSELUGO oral granules was within the range of that in patients administered KOSELUGO capsules.

No clinically relevant differences in the pharmacokinetics of selumetinib were observed following administration of a single-dose of either the granule or capsule dosage forms of KOSELUGO at equivalent dosages, under fasted and fed conditions, in healthy adults.

Absorption

Selumetinib absolute oral bioavailability is 62%. Selumetinib median (min, max) time to maximum plasma concentrations (Tmax) is 1.5 (0.22, 6.0) hours.

Effect of Food

No clinically significant differences in selumetinib pharmacokinetics were observed following administration of low fat (400-500 calories) or high-fat (800-1000 calories) meal.

Distribution

Selumetinib apparent volume of distribution across a dose range of 20 mg/m^2 to 30 mg/m^2 (0.8 to 1.2 times the recommended dosage) ranges from 40 L-3710 L (66).

The plasma protein binding is 98.4% (primarily albumin).

Elimination

Selumetinib elimination half-life is 9 (28) hours with an apparent (oral) clearance of 16 (44) L/hr/m^2.

Metabolism

Selumetinib is primarily metabolized by CYP3A4 and to a lesser extent by CYP2C19, CYP1A2, CYP2C9, CYP2E1, and CYP3A5. Selumetinib also undergoes glucuronidation by UGT1A1 and UGT1A3. It is estimated that 56% of the observed intrinsic clearance of selumetinib can be attributed to CYP metabolism and about 29% to direct glucuronidation by UGT enzymes.

The active metabolite, N desmethyl selumetinib, is generated by CYP2C19 and CYP1A2 with additional contribution by CYP2C9 and CYP2A6, and it is metabolized through the same routes as selumetinib.

N-desmethyl selumetinib represents < 10% of selumetinib levels in human plasma, but is approximately 3- to 5- times more potent than the parent compound, contributing to about 21% to 35% of the overall pharmacologic activity.

Excretion

After a single oral dose of radiolabeled selumetinib 75 mg (1.5-times the recommended dose) to healthy adults, 59% of the dose was recovered in feces (19% as unchanged) and 33% in urine (< 1% as parent).

Specific Populations

No clinically significant differences in the pharmacokinetics of selumetinib or N-desmethyl selumetinib were observed based on age (1-79 years) race [White (56%), Asian (22%), Black (19%)].

Pediatric Patients

No clinically significant differences in the pharmacokinetics of selumetinib or N-desmethyl selumetinib were observed between the pediatric (aged 1 to < 17 years) and adult patients.

Patients with Renal Impairment

No clinically significant differences in selumetinib exposures were observed in patients with end stage renal disease (CLcr < 15 mL/min) who required dialysis. CLcr was estimated using the Cockroft-Gault formula.

Patients with Hepatic Impairment

Dose normalized total AUC increased by 1.6-fold in patients with moderate hepatic impairment (Child-Pugh B) and in patients with severe hepatic impairment (Child-Pugh class C). Selumetinib unbound AUC increased by 1.4-fold in patients with moderate hepatic impairment (Child-Pugh B), and 3.2-fold in patients with severe hepatic impairment (Child-Pugh C).

Drug Interaction Studies

Clinical Studies and Model-Informed Approaches

Strong or Moderate CYP3A4 Inhibitors: Selumetinib AUC increased by 1.5-fold and Cmax by 1.2-fold following concomitant administration of itraconazole (strong CYP3A4 inhibitor). Concomitant use of erythromycin (moderate CYP3A4 inhibitor) is predicted to increase selumetinib AUC by 1.4-fold and Cmax by 1.2-fold.

Fluconazole: Selumetinib AUC increased by 1.5 fold and Cmax by 1.3 fold following concomitant administration of fluconazole (strong CYP2C19 inhibitor and moderate CYP3A4 inhibitor).

Strong or Moderate CYP3A4 Inducers: Selumetinib AUC decreased by 51% and Cmax by 26% following concomitant administration of rifampicin (strong CYP3A4 inducer). Concomitant use of efavirenz (moderate CYP3A4 inducer) is predicted to decrease selumetinib AUC by 38% and Cmax by 22%.

In Vitro Studies

CYP Enzymes: Selumetinib does not inhibit CYP1A2, CYP2A6, CYP2B6, CYP2C8, CYP2C9, CYP2C19, CYP2D6, CYP3A4, or CYP2E1. Selumetinib does not induce CYP3A4, CYP1A2, or CYP2B6.

Transporter Systems: Selumetinib does not inhibit BCRP, P-glycoprotein (P-gp), OATP1B1, OATP1B3, OCT2, OAT1, OAT3, MATE1, or MATE2K.

Selumetinib is a substrate of BCRP and P-gp.

13 NONCLINICAL TOXICOLOGY

13.1 Carcinogenesis, Mutagenesis, Impairment of Fertility

Carcinogenicity

Selumetinib was not carcinogenic in a 6-month study in rasH2 transgenic mice and in 2-year carcinogenicity study in rats at exposures ≥ 15 times the human exposure (AUC) at the clinical dose of 25 mg/m^2.

Mutagenicity

Selumetinib was not mutagenic or clastogenic in vitro. Selumetinib did result in an increase in micronucleated immature erythrocytes (chromosome aberrations) in mouse micronucleus studies, predominantly via an aneugenic mode of action, but at doses > 160 mg/kg (~38-times the human Cmax at the clinical dose of 25 mg/m^2).

Impairment of Fertility

In a 6-month mouse study, selumetinib did not affect male mating performance at any dose up to 20 mg/kg twice daily (approximately 33-times the human exposure based on AUC at the clinical dose of 25 mg/m^2 twice daily). In female mice exposed to selumetinib at 12.5 mg/kg twice daily, mating performance and fertility were not affected. The NOAEL for both maternal toxicity and effects on reproductive performance was 2.5 mg/kg twice daily (approximately 5-times the human exposure based on AUC at the clinical dose of 25 mg/m^2 twice daily).

13.2 Animal Toxicology and/or Pharmacology

In a 26-week repeat-dose toxicology study, selumetinib at a dose of 20 mg/kg (approximately 33-times the human exposure based on AUC at the clinical dose of 25 mg/m^2 twice daily) led to significant urinary tract obstruction as well as inflammation and luminal hemorrhage of the urethra leading to early death in male mice.

14 CLINICAL STUDIES

14.1 Neurofibromatosis Type 1 (NF1) with Inoperable Plexiform Neurofibromas (PN)

Pediatrics 2 18 years of Age (SPRINT Phase II Stratum 1)

The efficacy of KOSELUGO was evaluated in SPRINT Phase II Stratum 1, an-open label, multicenter, single arm trial (NCT01362803). Eligible patients were required to have NF1 with inoperable PN, defined as a PN that could not be completely removed without risk for substantial morbidity due to encasement of, or close proximity to, vital structures, invasiveness, or high vascularity of the PN. Patients were also required to have significant morbidity related to the target PN. Morbidities that were present in > 20% of patients included disfigurement, motor dysfunction, pain, airway dysfunction, visual impairment, and bladder/bowel dysfunction. Patients received KOSELUGO 25 mg/m^2 orally twice daily until disease progression or unacceptable toxicity.

The major efficacy outcome measure was overall response rate (ORR), defined as the percentage of patients with complete response (defined as disappearance of the target PN) or confirmed partial response (defined as ≥ 20% reduction in PN volume confirmed at a subsequent tumor assessment within 3-6 months). The target PN, defined as the PN that caused relevant clinical symptoms or complications (PN-related morbidities), was evaluated for response rate using centrally read volumetric magnetic resonance imaging (MRI) analysis per Response Evaluation in Neurofibromatosis and Schwannomatosis (REiNS) criteria. Tumor response was evaluated at baseline and while on treatment after every 4 cycles for 2 years, and then every 6 cycles. An additional efficacy outcome measure was duration of response (DoR).

A total of 50 pediatric patients received KOSELUGO. The median age was 10.2 years (range 3.5 to 17.4 years); 60% were male; and 84% were White, 8% were Black and 2% were Asian.

Efficacy results are provided in Table 14. The median time to onset of response was 7.2 months (range: 3.3 months to 1.6 years).

Table 14 Efficacy Results from SPRINT Phase II Stratum 1
Efficacy Parameter | SPRINT N = 50
Overall Response Rate [Responses required confirmation at least 3 months after the criteria for first response were met.] [The ORR assessment (data cut-off date [DCO]: June 2018) was conducted by a single National Cancer Institute reviewer who was a SPRINT investigator and who evaluated all PN imaging from patients enrolled at all trial sites.]
Overall Response Rate, n (%) | 33 (66%)
95% CI | (51, 79)
Complete Response [Complete response: disappearance of the target lesion; Partial response: decrease in target PN volume by ≥ 20% compared to baseline.] | 0
Confirmed Partial Response, n (%) | 33 (66%)
Duration of Response [DCO: March 2021.]
Median (95% CI) months | NR (41.2 – NE)
DoR ≥ 24 months, n (%) | 26 (79%)
DoR ≥ 36 months, n (%) | 21 (64%)
CI – confidence interval, DoR – duration of response, NE – not evaluable, NR – not reached.

An independent centralized review of tumor response per REiNS criteria (data cut-off June 2018) resulted in an ORR of 44% (95% CI: 30, 59).

Adults ≥ 18 years of Age (KOMET)

The efficacy of KOSELUGO in adult patients was evaluated in KOMET, a randomized, multicenter, double-blind, placebo-controlled trial (NCT04924608). Eligible patients were required to be 18 years of age or older with neurofibromatosis type 1 (NF1) and symptomatic, inoperable plexiform neurofibroma (PN). Inoperable plexiform neurofibroma (PN) is defined as a PN that could not be completely removed without risk for substantial morbidity due to encasement of, or close proximity to, vital structures, invasiveness, or high vascularity of the PN.

A total of 145 patients were randomized (1:1) to KOSELUGO 25 mg/m^2 (BSA) or placebo twice daily for 12 cycles (28-day cycles). After the end of Cycle 12, or earlier if disease progression was confirmed by the Independent Central Review (ICR), patients initially randomized to placebo crossed over to receive KOSELUGO in the open-label treatment phase. Treatment was discontinued if a patient was no longer deriving clinical benefit, experienced unacceptable toxicity, patient decision, PN progression, or at the discretion of the investigator.

One target and when applicable one non-target PN was assessed by using volumetric MRI analysis and REiNS criteria.

The major efficacy outcome measure was overall response rate (ORR) by the end of Cycle 16, as determined by ICR per REiNS criteria. Duration of response was an additional efficacy outcome measure.

The study demographics were 52% male, 56% White, 31% Asian, 6% Black or African American, 10% Hispanic or Latino ethnicity, and the median age was 29 years (range: 18 to 60 years). PN-related morbidities that were present in > 20% of patients included pain, motor dysfunction, and disfigurement.

The trial demonstrated statistically significant ORR in patients randomized to KOSELUGO compared to placebo by the end of Cycle 16. The median time to response was 3.7 months (range: 3.6 months to 11.2 months).

Efficacy results are shown in Table 15.

Table 15 Efficacy Results from KOMET
Efficacy Parameters | KOSELUGO; (N = 71) | Placebo; (N = 74)
Overall Response Rate by the end of Cycle 16 (ORR) [Patients with confirmed complete response or partial response by independent central review (ICR) per REiNS criteria. Response confirmation was by a consecutive scan within 3 to 6 months after the first response as determined by ICR per REiNS criteria.]
ORR % (95% CI) [All.Partial responders.] | 20 (11, 31) | 5 (2, 13)
p value [2-sided p-value calculated using Fisher’s exact method.] | 0.011
Duration of Response [Calculated using Kaplan-Meier method.]
Median (95% CI) months | NR (11.5, NE) | ND
≥ 6 months, n (%) | 12 (86%) | ND
CI – confidence interval, ND – Not determined for placebo arm, NE – not estimable, NR - not reached.

16 HOW SUPPLIED/STORAGE AND HANDLING

How Supplied

Selumetinib Capsules

Strength | Description | Capsules per Bottle | NDC Number
10 mg | White to off-white, opaque, hard capsule sealed with a clear band and marked with “SEL 10” in black ink. | 60 | 0310-0610-60
10 mg | White to off-white, opaque, hard capsule sealed with a clear band and marked with “SEL 10” in black ink. | 28 | 0310-0610-28
25 mg | Blue, opaque, hard capsule sealed with a clear band and marked with “SEL 25” in black ink. | 60 | 0310-0625-60
25 mg | Blue, opaque, hard capsule sealed with a clear band and marked with “SEL 25” in black ink. | 28 | 0310-0625-28

Selumetinib Oral Granules

Strength | Description | Capsules per Bottle | NDC Number
5 mg | Off‑white to light‑yellow free‑flowing oral granules contained within capsules. The capsules have a yellow cap and white body. The cap is printed with “sel 5” in black ink, and body is printed with a sprinkle capsule image indicating opening. | 60 | 0310‑0635‑60
7.5 mg | Off‑white to light‑yellow free‑flowing oral granules contained within capsules. The capsules have a pink cap and white body where the cap is printed with “sel 7.5” in black ink, and body is printed with a sprinkle capsule image indicating opening. | 60 | 0310‑0640‑60

Storage

KOSELUGO Capsules

Store KOSELUGO capsules at 20°C to 25°C (68°F to 77°F) with excursions permitted to 15°C to 30°C (59°F to 86°F) [see USP Controlled Room Temperature]. Dispense and store in the original bottle to protect from light and moisture. Do not remove desiccant. Keep the bottle tightly closed after first opening.

KOSELUGO Oral Granules

Store and transport KOSELUGO oral granules refrigerated at 2°C to 8°C (36°F to 46°F). After receipt, patients may store at room temperature 20°C to 25°C (68°F to 77°F). Do NOT exceed 30°C (86°F). KOSELUGO oral granules may clump together or stick to the capsule shell if exposed to high temperatures, which may lead to underdose. Dispense and store in the original bottle to protect from light and moisture. Do not remove desiccant. Keep the bottle tightly closed after first opening.

17 PATIENT COUNSELING INFORMATION

Advise the patient to read the FDA-approved patient labeling (Patient Information and Instructions for Use).

Left Ventricular Dysfunction

Advise patients and caregivers that KOSELUGO can cause a reduction in LVEF and to immediately report any signs or symptoms of cardiomyopathy to their healthcare provider [see Warnings and Precautions (5.1)].

Ocular Toxicity

Advise patients and caregivers that KOSELUGO can cause ocular toxicity that can lead to blindness and to contact their healthcare provider if the patient experiences any changes in their vision [see Warnings and Precautions (5.2)].

Gastrointestinal Toxicity

Advise patients and caregivers that KOSELUGO can cause diarrhea, nausea, vomiting, stomatitis and to contact their healthcare provider at the first sign of gastrointestinal toxicity [see Warnings and Precautions (5.3)].

Skin Toxicity

Advise patients and caregivers that KOSELUGO can cause serious skin toxicities and to contact their healthcare provider for severe skin changes [see Warnings and Precautions (5.4)].

Increased Creatine Phosphokinase

Advise patients and caregivers that KOSELUGO can cause increased CPK and to report any signs and symptoms of muscle pain or weakness to their healthcare provider [see Warnings and Precautions (5.5)].

Increased Vitamin E Levels and Increased Risk of Bleeding (KOSELUGO Capsules)

Advise patients and caregivers to notify their healthcare provider if they are taking a supplement containing vitamin E, a vitamin-K antagonist or an anti-platelet agent [see Warnings and Precautions (5.6)].

Embryo-Fetal Toxicity

- Advise pregnant women and females of reproductive potential of the potential risk to a fetus. Advise females of reproductive potential to inform their healthcare provider of a known or suspected pregnancy [see Warnings and Precautions (5.7), Use in Specific Populations (8.1)].
- Advise females of reproductive potential to use effective contraception during treatment with KOSELUGO and for 1 week after the last dose [see Use in Specific Populations (8.3)].
- Advise males with female partners of reproductive potential to use effective contraception during treatment with KOSELUGO and for 1 week after the last dose [see Use in Specific Populations (8.3), Nonclinical Toxicology (13.1)].

Lactation

Advise women not to breastfeed during treatment with KOSELUGO and for 1 week after the last dose [see Use in Specific Populations (8.2)].

Drug Interactions

Advise patients and caregivers to inform their healthcare provider of all concomitant medications, including prescription medicines, over-the-counter drugs, vitamins, and herbal products. Inform patients to avoid St. John’s wort, grapefruit or grapefruit juice, and Seville orange while taking KOSELUGO [see Drug Interactions (7)].

Dosing and Administration

Inform patients and caregivers on how to take KOSELUGO and what to do for missed or vomited doses [see Dosage and Administration (2.1)].

Distributed by:

AstraZeneca Pharmaceuticals LP

Wilmington, DE 19850

© AstraZeneca 2025

Patient Information

KOSELUGO® (ko-SEL-u-go)

(selumetinib)

capsules, for oral use

KOSELUGO® (ko-SEL-u-go)

(selumetinib)

oral granules

What is KOSELUGO?

KOSELUGO is a prescription medicine that is used to treat adults and children 1 year of age and older with neurofibromatosis type 1 (NF1) who have plexiform neurofibromas that cause symptoms and cannot be completely removed by surgery.

It is not known if KOSELUGO is safe and effective in children under 1 year of age.

Before taking KOSELUGO, tell your healthcare provider about all of your medical conditions, including if you:

- have heart problems.
- have eye problems.
- have liver problems.
- are pregnant or plan to become pregnant. KOSELUGO can harm your unborn baby.

Females who are able to become pregnant:

  ∘ Your healthcare provider should check to see if you are pregnant before you begin treatment with KOSELUGO.
  ∘ You should use effective birth control (contraception) during treatment with KOSELUGO and for 1 week after your last dose.
  ∘ Tell your healthcare provider right away if you become pregnant or think you may be pregnant during treatment with KOSELUGO.

Males with female partners who are able to become pregnant:

  ∘ You should use effective birth control (contraception) during treatment with KOSELUGO and for 1 week after your last dose.
- are breastfeeding or plan to breastfeed. It is not known if KOSELUGO passes into your breast milk.
  ∘ Do not breastfeed during treatment with KOSELUGO and for 1 week after your last dose.
  ∘ Talk to your healthcare provider about the best way to feed your baby during this time.

Tell your healthcare provider about all the medicines you take, including prescription and over-the-counter medicines, vitamins, or herbal supplements. Certain medicines may affect the way KOSELUGO works.

Especially tell your healthcare provider if you are taking a supplement containing vitamin E, aspirin, blood thinners, or other medicines to treat blood clots. KOSELUGO capsules contain vitamin E, which may increase your risk of bleeding.

How should I take KOSELUGO?

- Take or give KOSELUGO exactly as your healthcare provider tells you to.
- Do not change your dose or stop taking KOSELUGO unless your healthcare provider tells you to.
- Your healthcare provider will decide on the right dose of KOSELUGO based on your or your child’s weight or size (body surface area).
- Take or give KOSELUGO 2 times a day.
- If you or your child miss a dose of KOSELUGO capsules or KOSELUGO oral granules, take or give the dose as soon as you remember, unless the next dose is due within 6 hours. If your scheduled dose is due within 6 hours, skip the dose and take or give the next dose at the regular time.
- If you or your child vomit after taking a dose of KOSELUGO capsules or KOSELUGO oral granules, do not take an additional dose. Take the next dose at the regular scheduled time.

KOSELUGO comes in capsules and oral granules.

- If your healthcare provider prescribes KOSELUGO capsules:
  ∘ Take KOSELUGO capsules with or without food.
  ∘ Swallow KOSELUGO capsules whole. Do not open, chew, or crush the capsules.
  ∘ Tell your healthcare provider if you or your child has trouble swallowing capsules.
- If your healthcare provider prescribes KOSELUGO oral granules:
  ∘ See the Instructions for Use for the instructions on how to prepare and take or give KOSELUGO oral granules.
  ∘ Prepare KOSELUGO oral granules by carefully opening the capsule and sprinkling all of the oral granules on a small amount (about 1 to 3 teaspoons) of smooth yogurt, or fruit puree containing the following fruits: apple, banana, pear, or strawberry.
  ∘ Take or give the KOSELUGO oral granules and food mixture within 30 minutes of preparing the dose.
  ∘ If the prepared dose of KOSELUGO oral granules and food mixture is not taken or given within 30 minutes, do not take or give the prepared dose. Throw away the mixture and prepare a new dose.
  ∘ If part of a dose is taken or given within 30 minutes of preparing, throw away the remainder of the mixture and do not prepare a new dose. Take or give the full dose within 30 minutes next time.
  ∘ The KOSELUGO oral granules should flow freely. Do not use if the oral granules are clumped or stuck inside the capsule shell. Contact your pharmacy if this happens.
  ∘ Throw away the empty capsule shells after use.
  ∘ Do not swallow, chew, or dissolve the capsule shells of KOSELUGO oral granules.
  ∘ Do not chew or crush the KOSELUGO oral granules. Do not add oral granules to liquids.
  ∘ Do not mix KOSELUGO oral granules in grapefruit or any juice, fruit puree or jam containing Seville orange.

What should I avoid while taking KOSELUGO?

Avoid St John’s wort, grapefruit or grapefruit juice, and Seville orange during treatment with KOSELUGO.

What are the possible side effects of KOSELUGO?

KOSELUGO can cause serious side effects, including:

- Heart problems. KOSELUGO can lower the amount of blood pumped by your heart, which can be severe. Your healthcare provider will do tests before and during treatment with KOSELUGO to check how well your heart is working. Tell your healthcare provider right away if you get any of the following signs or symptoms:

∘ persistent coughing or wheezing
∘ shortness of breath
∘ swelling of your ankles and feet

∘ tiredness
∘ increased heart rate

- Eye problems. KOSELUGO can cause eye problems that can lead to blindness. Your healthcare provider will check your vision before and during treatment with KOSELUGO. Tell your healthcare provider right away if you get new or worsening vision changes, including:

∘ blurred vision
∘ loss of vision

∘ dark spots in your vision (floaters)
∘ other changes to your vision

- Stomach, intestine, and mouth (gastrointestinal) problems. KOSELUGO can cause diarrhea, vomiting, nausea, and mouth sores. Diarrhea can be severe with KOSELUGO. Tell your healthcare provider right away the first time that you get diarrhea during treatment with KOSELUGO. Your healthcare provider may give you medicine to help control your diarrhea and may tell you to drink more fluids.
- Skin problems. Koselugo can cause severe skin rashes. Tell your healthcare provider if you get any of the following signs of skin problems:

∘ rash that covers a large area of your body
∘ flat skin rash
∘ raised bumps on your skin
∘ skin bumps that look like acne

∘ blisters
∘ peeling skin
∘ itchy rash
∘ hair thinning or hair loss (alopecia)

Increased level of an enzyme called creatine phosphokinase (CPK) in your blood and muscle problems. Koselugo can cause severe muscle problems. Treatment with KOSELUGO may increase the level of enzyme in your blood called creatine phosphokinase (CPK), which may be a sign of muscle damage. Increased level of CPK in the blood are common during treatment with KOSELUGO and can also be severe. Your healthcare provider should do a blood test to check your blood levels of CPK before and during treatment with KOSELUGO. Tell your healthcare provider right away if you get any of the following signs or symptoms:

  ∘ muscle aches or pain
  ∘ muscle spasms and weakness

∘ dark, reddish urine

Your healthcare provider may change your dose, temporarily stop, or permanently stop treatment with KOSELUGO if you have any of these side effects.

The most common side effects of KOSELUGO in children include:

  - vomiting
  - diarrhea
  - increased level of an enzyme called creatine phosphokinase (CPK) in your blood
  - dry skin

- redness around the fingernails
- nausea
- skin bumps that look like acne
- fever

The most common side effects of KOSELUGO in adults include:

- rash
- diarrhea

- skin bumps that look like acne

These are not all of the possible side effects of KOSELUGO.

Call your doctor for medical advice about side effects. You may report side effects to FDA at 1-800-FDA-1088.

How should I store KOSELUGO?

- Store KOSELUGO capsules and KOSELUGO oral granules at room temperature between 68°F to 77°F (20°C to 25°C).
- Do not store KOSELUGO oral granules above 86°F (30°C). Store KOSELUGO oral granules in the refrigerator between 36°F to 46°F (2°C to 8°C) if the temperature is above 86°F (30°C). KOSELUGO oral granules may clump together or stick to the capsule shell if the medicine gets too hot, and you may not get your full dose.
- Keep KOSELUGO oral granules cold in a cooler bag with a cold pack if you need to take it anywhere.
- The bottle of KOSELUGO capsules and KOSELUGO oral granules contain a desiccant packet to reduce moisture. Do not throw away the desiccant packet.
- Keep KOSELUGO capsules and KOSELUGO oral granules in its original bottle to protect from light and moisture. Keep the bottle tightly closed.

Keep KOSELUGO and all medicines out of the reach of children.

General information about the safe and effective use of KOSELUGO.

Medicines are sometimes prescribed for purposes other than those listed in a Patient Information leaflet. Do not use KOSELUGO for a condition for which it was not prescribed. Do not give KOSELUGO to other people, even if they have the same symptoms you have. It may harm them. You can ask your pharmacist or healthcare provider for information about KOSELUGO that is written for a healthcare professional.

What are the ingredients in KOSELUGO?

Active ingredient: selumetinib.

KOSELUGO capsule inactive ingredients:

- The 10 mg and 25 mg capsules contain: vitamin E polyethylene glycol succinate.
- The 10 mg capsule shell contains: carnauba wax, carrageenan, hypromellose, potassium chloride, purified water, and titanium dioxide.
- The 10 mg capsule printing ink contains: ammonium hydroxide, iron oxide black, propylene glycol, and shellac.
- The 25 mg capsule shell contains: carnauba wax and/or corn starch, carrageenan, FD&C blue 2, ferric oxide yellow, hypromellose, potassium chloride, purified water, and titanium dioxide.
- The 25 mg capsule printing ink contains: carnauba wax, FD&C Blue 2 aluminum lake, ferric oxide red, ferric oxide yellow, glyceryl monooleate, and shellac.

KOSELUGO oral granule inactive ingredients:

- The 5 mg and 7.5 mg uncoated cores contain: glyceryl dibehenate and stearoyl polyoxylglycerides.
- The 5 mg and 7.5 mg granule coatings contain: acetone, hypromellose acetate succinate, and stearic acid.
- The 5 mg shell contains: ferric oxide yellow, hypromellose, and titanium dioxide.
- The 5 mg printing ink contains: butyl alcohol, dehydrated alcohol, ferric oxide black, isopropyl alcohol, potassium hydroxide, propylene glycol, purified water, shellac, and strong ammonia solution.
- The 7.5 mg shell contains: ferric oxide red, hypromellose, and titanium dioxide.
- The 7.5 mg printing ink contains: butyl alcohol, dehydrated alcohol, ferric oxide black, isopropyl alcohol, potassium hydroxide, propylene glycol, purified water, shellac, and strong ammonia solution.

Distributed by: AstraZeneca Pharmaceuticals LP, Wilmington, DE 19850

©AstraZeneca 2025

For more information, go to website www.KOSELUGO.com or call 1-800-236-9933

This Patient Information has been approved by the U.S. Food and Drug Administration. Revised: 11/2025

Instructions for Use

KOSELUGO® (ko-SEL-u-go)

(selumetinib)

oral granules

This Instructions for Use contains information on how to take or give KOSELUGO oral granules.

Read this Instructions for Use before taking or giving KOSELUGO oral granules and each time you get a refill. There may be new information. This information does not take the place of talking to your healthcare provider about your or your child’s medical condition or treatment. Talk to your healthcare provider or pharmacist if you have any questions about how to take or give KOSELUGO oral granules.

Important Information You Need to Know Before Taking or Giving KOSELUGO oral granules

- KOSELUGO oral granules come in capsules that must be opened before use. Do not swallow, chew, or dissolve the capsule shells. Do not chew or crush the oral granules. Do not add oral granules to liquids.
- Take or give KOSELUGO oral granules exactly as your healthcare provider tells you to.
- Do not change your dose or stop taking KOSELUGO oral granules unless your healthcare provider tells you to.
- Your healthcare provider will decide on the right dose of KOSELUGO based on your or your child’s weight or size (body surface area).
- KOSELUGO oral granules come in 2 different strengths: 5 mg and 7.5 mg. Each strength is a different color. Your healthcare provider may prescribe more than 1 strength of KOSELUGO oral granules for your or your child’s dose. Make sure that you understand how many capsules of KOSELUGO oral granules you need and what strengths to take.
- Your healthcare provider may change the dose, temporarily stop, or permanently stop treatment with KOSELUGO oral granules if you or your child has side effects.
- Take or give KOSELUGO oral granules 2 times a day.
- If you or your child miss a dose of KOSELUGO oral granules, take or give the dose as soon as you remember, unless the next dose is due within 6 hours. If your scheduled dose is due within 6 hours, skip the dose and take or give the next dose at the regular time.
- If you or your child vomits after taking a dose of KOSELUGO oral granules, do not take an additional dose. Take the next dose at the regular scheduled time.
- For more information about KOSELUGO oral granules, see the Patient Information leaflet.

Supplies needed to prepare a dose of KOSELUGO oral granules:

- The prescribed number of KOSELUGO oral granules.
- Smooth yogurt, or fruit puree containing the following fruits: apple, banana, pear, or strawberry.
- A spoon or a small cup.
- A paper towel or plate.

Preparing KOSELUGO oral granules

Step 1: Wash and dry your hands thoroughly.

Step 2: Open the bottle(s) and take out the number of capsule(s) needed for your prescribed dose of KOSELUGO oral granules.

Step 3: Add a small amount (about 1 to 3 teaspoons) of smooth yogurt, or fruit puree containing apple, banana, pear, or strawberry onto the spoon or into a small cup.

- Do not mix KOSELUGO oral granules in grapefruit or any juice, fruit puree or jam containing Seville orange.

Step 4: Place the spoon or cup on the paper towel or plate. Carefully open the capsule(s) one at a time and sprinkle the entire contents of the capsule (oral granules) onto the food that is on the spoon or in the small cup.

- If you are using a spoon to prepare KOSELUGO oral granules, you may find it easier to prepare and take or give 1 capsule at a time. Repeat Steps 3 to 6 for each capsule until the full dose is taken or given.
- Do not swallow, chew, or dissolve the capsule shells. Do not chew or crush the oral granules. Do not add oral granules to liquids.

Important: The oral granules should flow freely inside the capsule. Do not use the capsule if the oral granules are clumped or stuck inside the capsule shell. Contact your pharmacy if this happens.

Taking or giving KOSELUGO oral granules

Step 5: Take or give the KOSELUGO oral granules and food mixture within 30 minutes of preparing the dose. Swallow the mixture without chewing while seated upright. Do not save for future use.

Note:

- If you do not take or give the KOSELUGO oral granules and food mixture within 30 minutes of preparing the dose, do not take or give the mixture. Throw away the mixture and prepare a new dose.
- If you take or give part of the mixture within 30 minutes of preparing the dose, throw away the remainder of the mixture and do not prepare a new dose. Take or give the full dose within 30 minutes next time.

Step 6: If you used a cup to prepare KOSELUGO oral granules, add more of the same food into the cup and take or give all of the mixture to make sure you get the full dose.

Clean up

- Throw away empty capsule shells, used paper towel, and any spilled oral granules in your household trash.
- Wash your hands and all the supplies used to take or give KOSELUGO oral granules.

Storing KOSELUGO oral granules

- Store KOSELUGO oral granules at room temperature between 68°F to 77°F (20°C to 25°C).
- Do not store KOSELUGO oral granules above 86°F (30°C). Store KOSELUGO oral granules in the refrigerator between 36°F to 46°F (2°C to 8°C) if the temperature is above 86°F (30°C). KOSELUGO oral granules may clump together or stick to the capsule shell if the medicine gets too hot, and you may not get your full dose.
- Keep KOSELUGO oral granules cold in a cooler bag with a cold pack if you need to take it anywhere.
- The bottle of KOSELUGO oral granules contains a desiccant packet to reduce moisture. Do not throw away the desiccant packet.
- Keep KOSELUGO oral granules in its original bottle to protect from light and moisture. Keep the bottle tightly closed.

Keep KOSELUGO and all medicines out of the reach of children.

Disposing of KOSELUGO oral granules

- Ask your pharmacist how to throw away unused doses, expired medicines, or medicines you no longer use.

Distributed by: AstraZeneca Pharmaceuticals LP, Wilmington, DE 19850

©AstraZeneca 2025

For more information, go to website www.KOSELUGO.com or call 1-800-236-9933.

This Instructions for Use has been approved by the U.S. Food and Drug Administration. Approved: Sep/2025

PACKAGE/LABEL PRINCIPAL DISPLAY PANEL 10mg

NDC 0310-0610-28

Koselugo®

(selumetinib)

capsules

10 mg

Rx only

Dispense in original bottle. Do not remove

desiccant. Protect from moisture.

Keep the bottle tightly closed.

28 Capsules AstraZeneca

PACKAGE/LABEL PRINCIPAL DISPLAY PANEL 25mg

NDC 0310-0625-28

Koselugo®

(selumetinib)

capsules

25 mg

Rx only

Dispense in original bottle. Do not remove

desiccant. Protect from moisture.

Keep the bottle tightly closed.

28 Capsules AstraZeneca

Package/Label Display Panel 5 mg

NDC 0310-0635-60

Koselugo®

(selumetinib)

Oral granules

7.5 mg

Sprinkle oral granules on or mix

with smooth yogurt or fruit puree.

Dispense and store in original

bottle below 25° C (77°F) to

protect from light and moisture.

60 Capsules

Rx only Astrazeneca

Package/Label Display Panel 7.5 mg

NDC 0310-0640-60

Koselugo®

(selumetinib)

Oral granules

7.5 mg

Sprinkle oral granules on or mix

with smooth yogurt or fruit puree.

Dispense and store in original

bottle below 25° C (77°F) to

protect from light and moisture.

60 Capsules

Rx only Astrazeneca